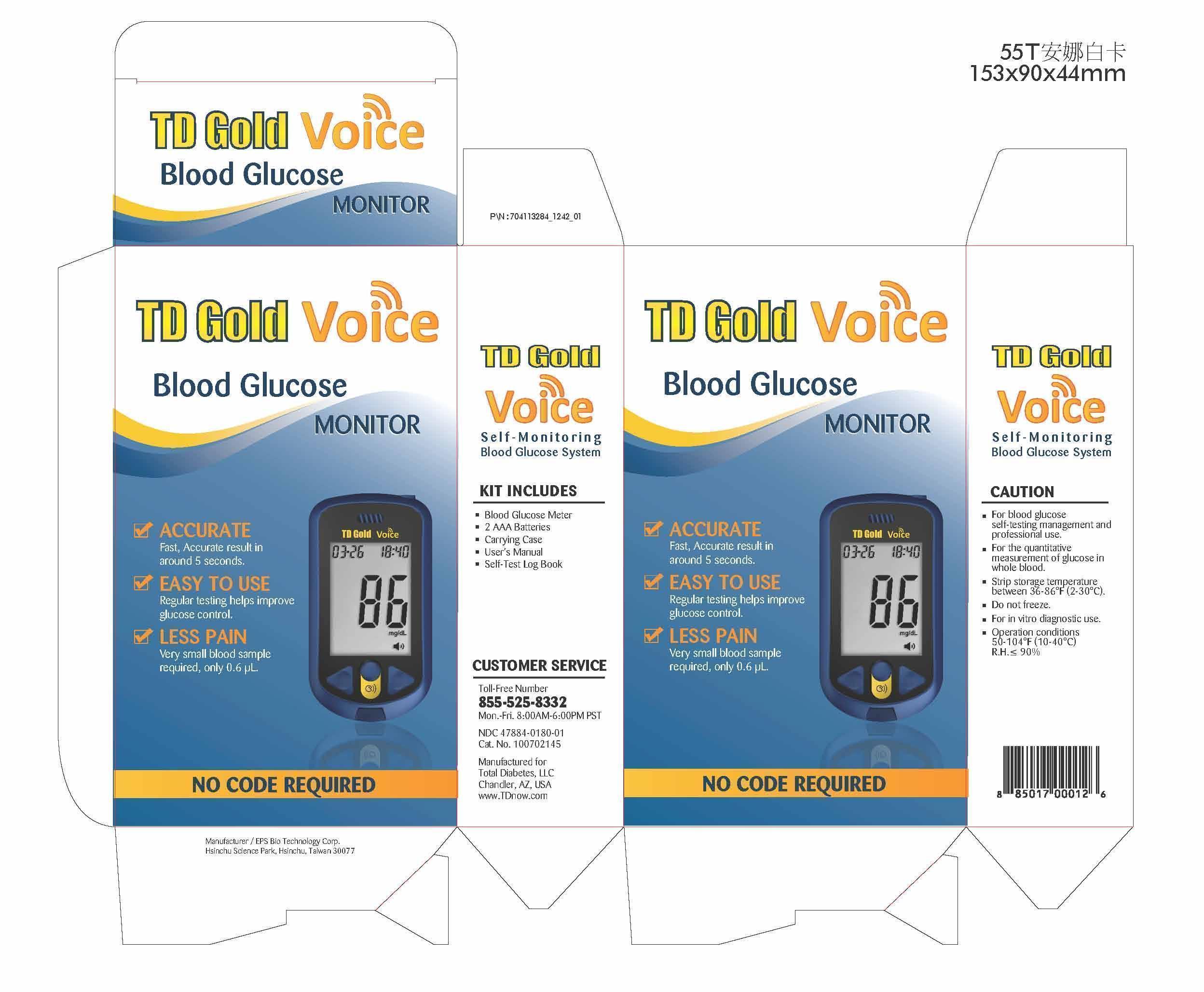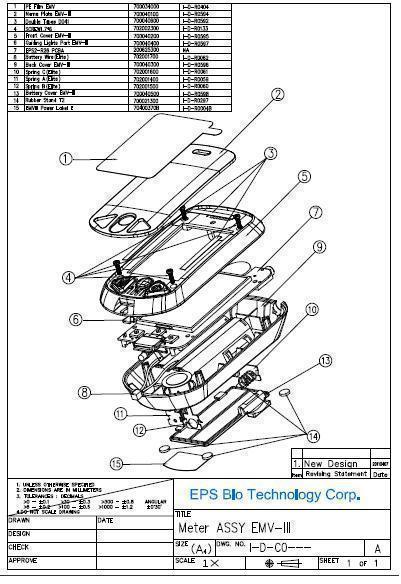 DRUG LABEL: TD Gold Voice Blood Glucose Monitor
NDC: 47884-180
Manufacturer: EPS Bio Technology Corp.
Category: other | Type: MEDICAL DEVICE
Date: 20130910

Home Use Medical Device: TD Gold Voice Self-monitoing Blood Glucose System